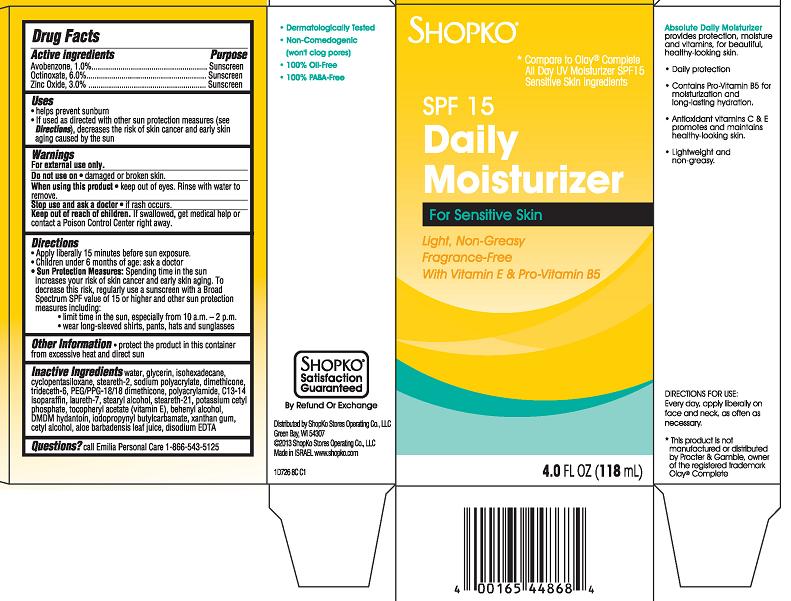 DRUG LABEL: ShopKo Absolute Daily Moisturizer SPF15 Sensitive Skin
NDC: 37012-726 | Form: CREAM
Manufacturer: Shopko Stores Operating Co., LLC
Category: otc | Type: HUMAN OTC DRUG LABEL
Date: 20130506

ACTIVE INGREDIENTS: OCTINOXATE 6 mg/100 mL; ZINC OXIDE 3 mg/100 mL; AVOBENZONE 1 mg/100 mL
INACTIVE INGREDIENTS: WATER; GLYCERIN; ISOHEXADECANE; CYCLOMETHICONE 5; STEARETH-2; POLYACRYLAMIDE (10000 MW); C13-14 ISOPARAFFIN; LAURETH-7; SODIUM POLYACRYLATE (2500000 MW); DIMETHICONE; TRIDECETH-6; PEG/PPG-18/18 DIMETHICONE; STEARYL ALCOHOL; POTASSIUM CETYL PHOSPHATE; STEARETH-21; .ALPHA.-TOCOPHEROL ACETATE; DOCOSANOL; DMDM HYDANTOIN; IODOPROPYNYL BUTYLCARBAMATE; CETYL ALCOHOL; XANTHAN GUM; ALOE VERA LEAF; EDETATE DISODIUM

SHOPKO SPF15 Daily Moisturizer for Sensitive Skin

Active ingredient

Avobenzone 1.0%

Octinoxate 6.0%

Zinc Oxide 3.0%

Purpose

Sunscreen

Uses

- helps prevent sunburn
- If used as directed with other sun protection measures (see Directions), decreases the risk of skin cancer and early skin aging caused by the sun

Warnings

For external use only.

Do not use on

- damaged or broken skin.

When using this product

- keep out of eyes. Rinse with water to remove.

Stop use and ask a doctor

- if rash occurs.

Keep Out of Reach of Children.

If swallowed, get medical help or contact a Poison Control Center right away.

Directions

- Apply liberally 15 minutes before sun exposure.
- Children under 6 months of age: ask a doctor
- Sun Protection Measures: Spending time in the sun increases your risk of skin cancer and early skin aging. To decrease this risk, regularly use a sunscreen with a Broad Spectrum SPF value of 15 or higher and other sun protection measures including:
  - limit time in the sun, especially from 10 a.m. - 2 p.m.
  - wear long-sleeved shirts, pants, hats and sunglasses

Other Information

- protect the product in this container from excessive heat and direct sun

Inactive Ingredients

water, glycerin, isohexadecane, cyclopentasiloxane, steareth-2, sodium polyacrylate, dimethicone, trideceth-6, PEG/PPG-18/18 dimethicone, polyacrylamide, C13-14 isoparaffin, laureth-7, stearyl alcohol, steareth-21, potassium cetyl phosphate, tocopheryl acetate (vitamin E), behenyl alcohol, DMDM hydantoin, iodopropynyl butylcarbamate, xanthan gum, cetyl alcohol, aloe barbadensis leaf juice, disodium EDTA

Package/Label Principal Display Panel - Carton Label

Shopko*

*Compare to Olay® Complete All Day UV Moisturizer SPF15 Sensitive Skin Ingredients

SPF 15 Daily Moisturizer For Sensitive Skin
Light, Non-Greasy
Fragrance-Free
With Vitamin E & Pro-Vitamin B5

- Dermatologically Tested
- Non-Comedogenic (won't clog pores)
- 100% Oil-Free
- 100% PABA-Free

Absolute Daily Moisturizer provides protection, moisture and vitamins, for beautiful, health-looking skin.

- Daily protection.
- Contains Pro-Vitamin B5 for moisturization and long-lasting hydration.
- Antioxidant vitamins C & E promotes and maintains healthy-looking skin.
- Lightweight and non-greasy.

DIRECTIONS FOR USE: Every day, apply liberally on face and neck, as often as necessary.

*This product is not manufactured or distributed by Procter & Gamble, owner of the registered trademark Olay® Complete

4 FL OZ (118 mL)

Distributed by ShopKo Stores Operating Co., LLC
Green Bay, WI 54307
© 2013 ShopKo Stores Operating Co., LLC
Made in Israel. www.shopko.com

1D726 8C C1

Carton Label